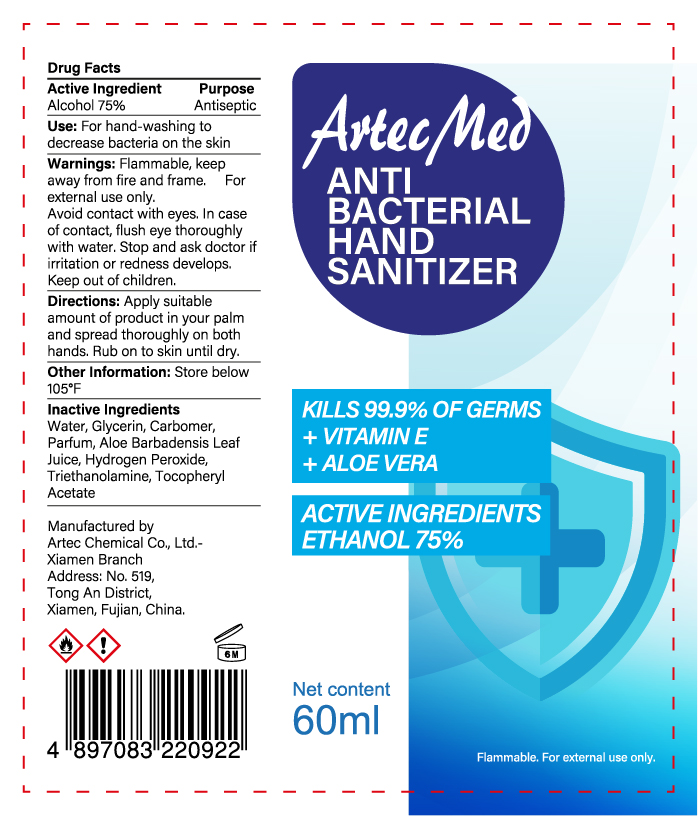 DRUG LABEL: Artec Med Antibacterial Hand Sanitizer
NDC: 76352-101 | Form: SOLUTION
Manufacturer: Artec Chemical Company Limited
Category: otc | Type: HUMAN OTC DRUG LABEL
Date: 20200515

ACTIVE INGREDIENTS: ALCOHOL 75 mL/100 mL
INACTIVE INGREDIENTS: WATER; GLYCERIN; ALOE VERA LEAF; .ALPHA.-TOCOPHEROL ACETATE; CARBOMER 934; TROLAMINE; HYDROGEN PEROXIDE

NA

Active Ingredient(s)

Ethyl Alcohol 75% v/v

Purpose

Antiseptic

Use

For hand washing to decrease bacteria on the skin

Warnings

Flammable. Keep away from fire and flame

For external use only.

When using this product, avoid contact with eyes. In case of contact, flush eyes thoroughly with water

Stop use and ask a doctor if irritation or redness develops

Keep out of reach of children

Directions

Apply suitable amount of product in your palm and spread thoroughly on both hands. Rub onto skin until dry

Other information

Store below 105F

Inactive ingredients

Water, Glycerin, Parfum, Aloe Barbadensis Leaf Juice, Hydrogen Peroxide, Triethanolamine, Tocopheryl Acetate